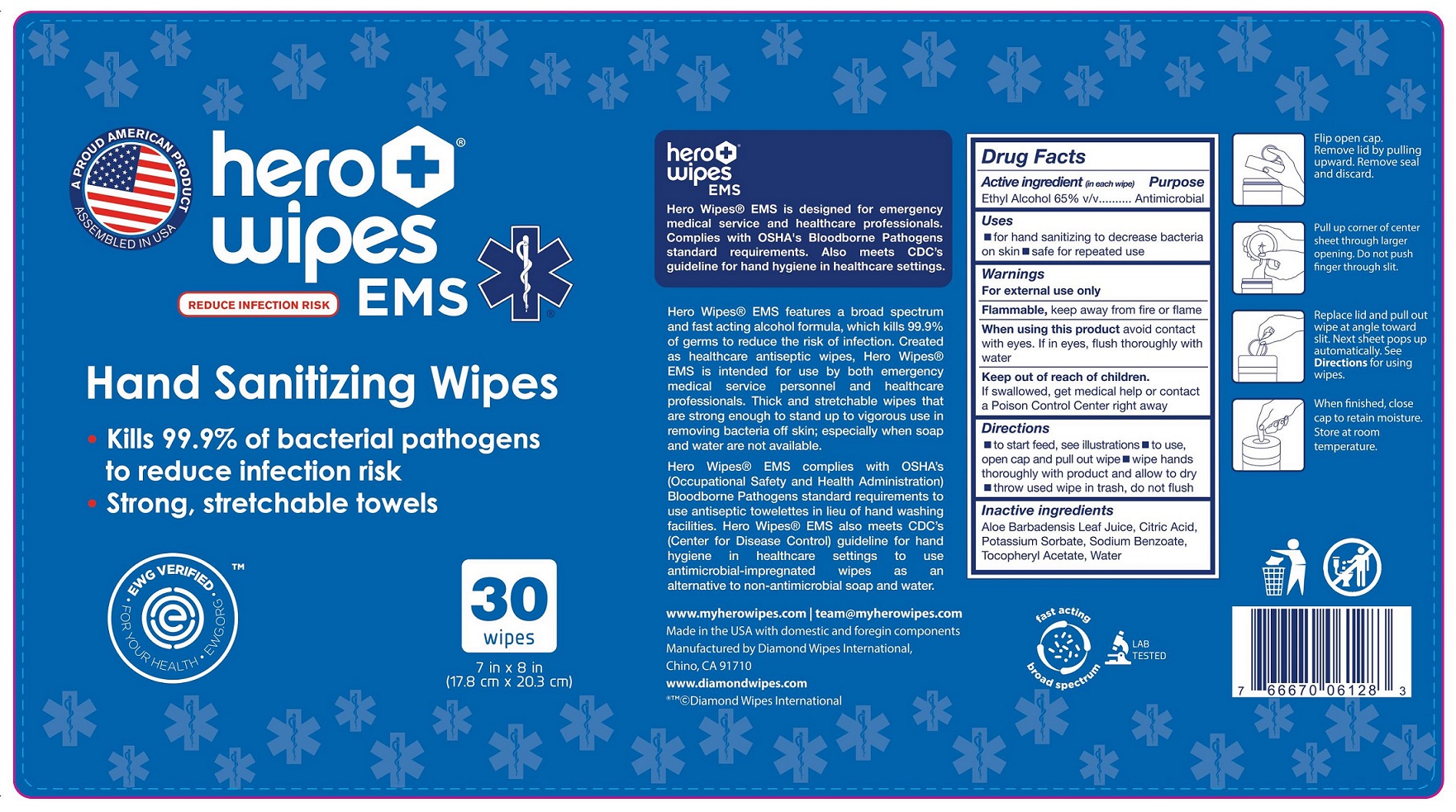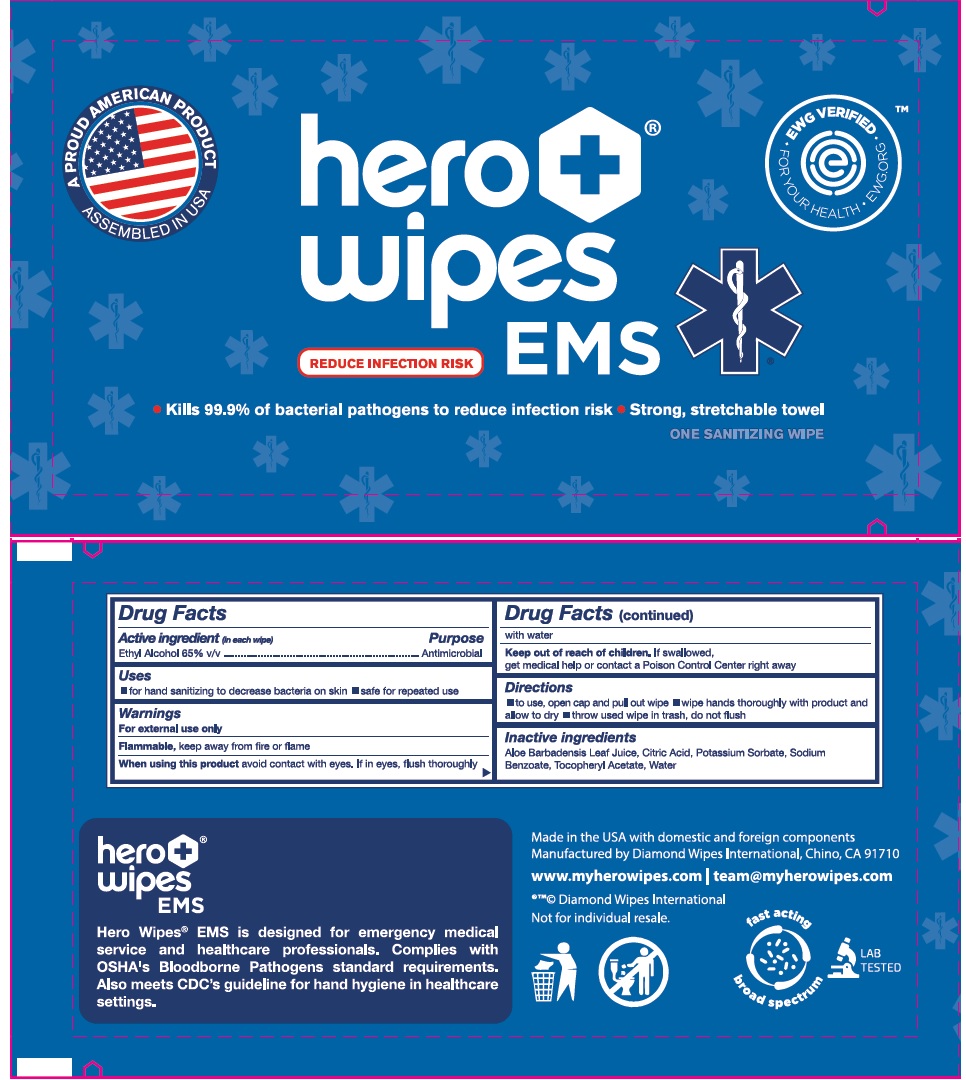 DRUG LABEL: Hero Wipes EMS Hand Sanitizer
NDC: 64709-156 | Form: Cloth
Manufacturer: Diamond Wipes International, Inc.
Category: otc | Type: HUMAN OTC DRUG LABEL
Date: 20200318

ACTIVE INGREDIENTS: alcohol 65 mL/1 mL
INACTIVE INGREDIENTS: WATER; ALOE VERA LEAF; .ALPHA.-TOCOPHEROL ACETATE, DL-

Active ingredients

Ethyl Alcohol 65% v/v

Purpose

Antimicrobial

Uses

- For hand sanitizing to decrease bacteria on skin
- reccomended for repeated use

Warnings

For external use only

Flammable: Keep away from fire or flame

When using this product

avoid contact with eyes. If in eyes, flush thoroughly with water

Keep out of reach of children

If swallowed, get medical help or contact a Poison Control Center right away

Directions

- To start feed, see illustrations
- to use open cap and pull out wipe
- wipe hands thoroughly with product and let hands air dry
- throw used wipe in trash
- do not flush

Inactive Ingredients

Aloe Barbadensis leaf juice, citric acid, potassium sorbate, sodium benzoate, tocopheryl acetate, water

PACKAGE LABEL

Hero Wipes EMS

Reduce infection risk

Kills 99.9 of baterial pathogens to reduce infection risk

Stong stretchable towel

Singles

CCanister